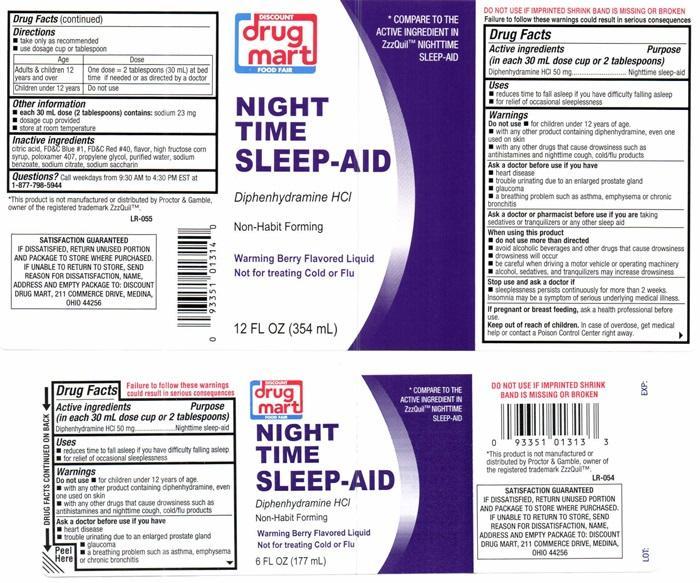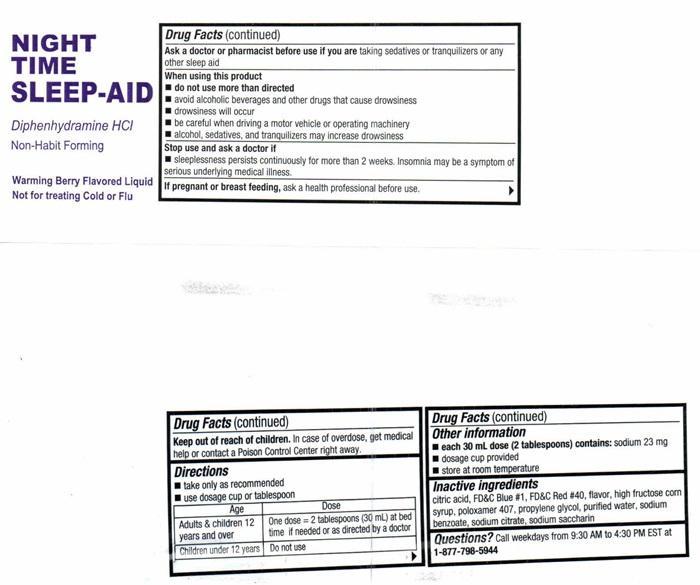 DRUG LABEL: NIGHT TIME SLEEP-AID
NDC: 53943-522 | Form: LIQUID
Manufacturer: Discount Drug Mart
Category: otc | Type: HUMAN OTC DRUG LABEL
Date: 20251223

ACTIVE INGREDIENTS: DIPHENHYDRAMINE HYDROCHLORIDE 50 mg/30 mL
INACTIVE INGREDIENTS: ANHYDROUS CITRIC ACID; FD&C BLUE NO. 1; FD&C RED NO. 40; HIGH FRUCTOSE CORN SYRUP; POLOXAMER 407; PROPYLENE GLYCOL; WATER; SODIUM BENZOATE; SODIUM CITRATE; SACCHARIN SODIUM

Drug Facts Active ingredients (in each 30 mL dose cup or 2 tablespoons)

Diphenhydramine HCL 50 mg

Purpose

Nighttime sleep-aid

Kep out of reach of children

Keep out of reach of children. In case of overdose, get medical help or contact a Poison Control Center right away.

Uses

- reduces time to fall asleep if you have difficulty falling asleep
- for relief of occassional sleeplessness

Warnings

DO NOT USE IF IMPRINTED SHRINK BAND IS MISSING OR BROKEN

Failure to follow these warnings could result in serious consequences.

Do not use

- for children under 12 years of age.
- with any other product containing diphenhydramine, even one used on skin
- with any other drugs that cause drowsiness such as antihistamines and nighttime cough, cold/flu products

Ask a doctor before use if you have

- heart disease
- trouble urinating due to an enlarged prostate gland
- glaucoma
- a breathing problem such as asthma, emphysema or chronic bronchitis

Ask a doctor or pharmacist before use if you are

taking sedatives or tranquilizers or any other sleep aid

When using this product

- do not use more than directed
- avoid alcoholic beverages and other drugs that cause drowsiness
- drowsiness will occur
- be careful driving a motor vehicle or operating machinery
- alcohol, sedatives, and tranquilizers may increase drowsiness

Stop use and ask a doctor if

sleeplessness persists continously for more than 2 weeks. Insomnia may be a symptom of serious underlying medical illness.

If pregnant or breast feeding,

ask a health professional before use.

Directions

- take only as recommended
- use dosage cup or tablespoon

Age | Dose
Adults and children 12 years and over | One dose = 2 tablespoons (30 mL) at bedtime if needed or as directed by a doctor
Children under 12 years | Do not use

Other information

- each 30 mL dose (2 tablespoons) contains: sodium 23 mg
- dosage cup provided
- store at room temperature

Inactive ingredients

citric acid, FD and C Blue # 1, FD and C Red # 40, flavor, high fructose corn syrup, poloxamer 407, propllene glycol, purified water, sodium benzoate, sodium citrate, sodium saccharin

Questions?

Call weekdays from 9:30 AM to 4:30 PM EST at 1-877-798-5944

DISCOUNT drug mart FOOD FAIR NIGHT TIME SLEEP-AID product label

* COMPARE TO THE ACTIVE INGREDIENT IN ZzzQuil™NIGHTTIME SLEEP-AID

DISCOUNT

drug mart

FOOD FAIR

NIGHT TIME SLEEP-AID

Diphenhydramine HCL

Non-Habit Forming

Warming Berry Flavored Liquid

Not for treating Cold or Flu

12 FL OZ (354 mL)

* This product is not manufactured or distributed by Proctor and Gamble owner of the registered trademark ZzzQuil™

LR-055

SATISFACTION GUARANTEED

IF DISSATISFIED, RETURN UNUSED PORTION AND PACKAGE TO THE STORE WHERE PURCHASED. IF UNABLE TO RETURN TO THE STORE, SEND REASON FOR DISSATISFACTION , NAME, ADDRESS AND EMPTY PACKAGE TO: DISCOUNT DRUG MART, 211 COMMERCE DRIVE MEDINNA, OHIO 44256

res